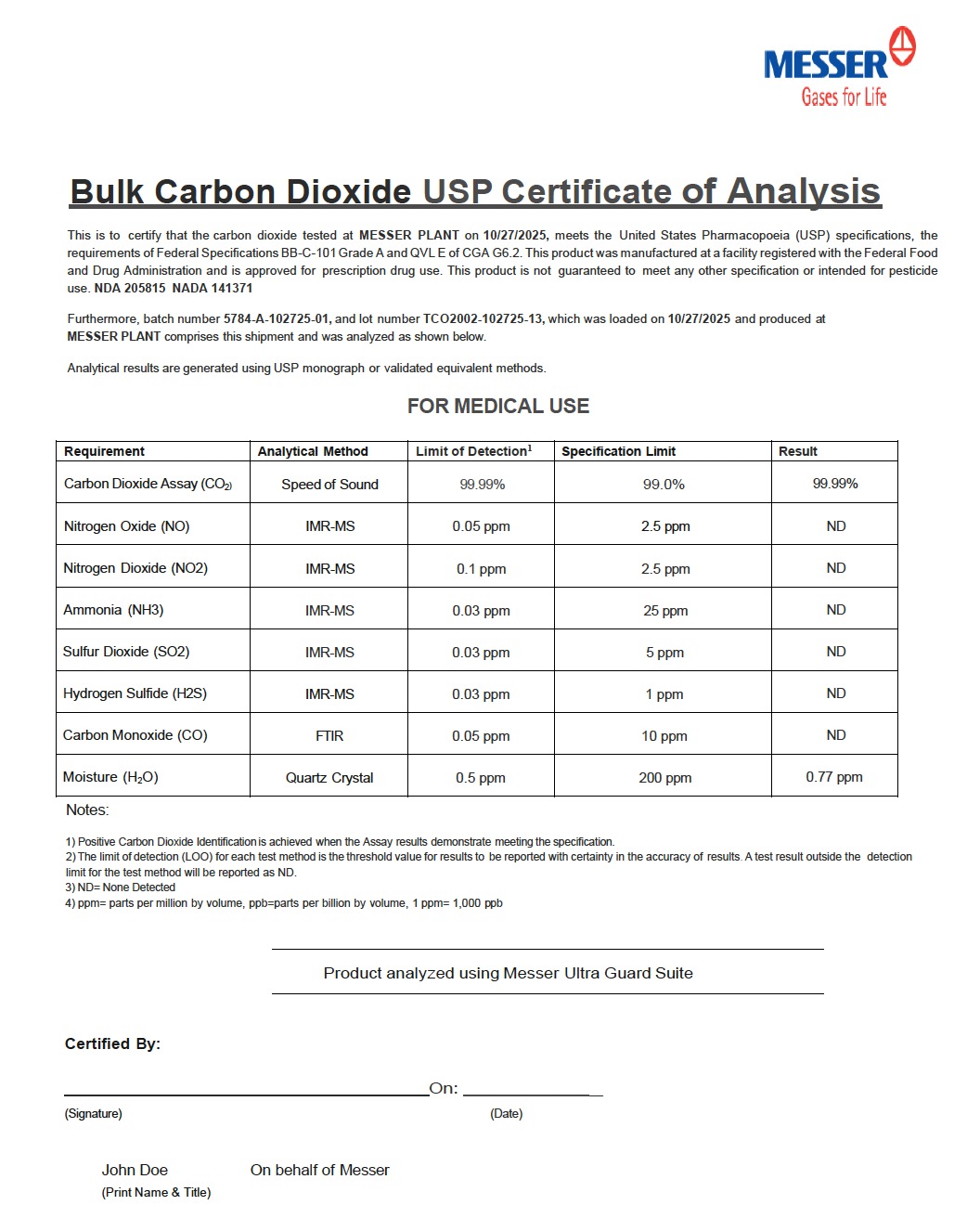 DRUG LABEL: Carbon Dioxide
NDC: 45149-914 | Form: GAS
Manufacturer: Messer Merchant Production LLC
Category: animal | Type: PRESCRIPTION ANIMAL DRUG LABEL
Date: 20251114

ACTIVE INGREDIENTS: CARBON DIOXIDE 990 mL/1 L

Carbon Dioxide Refrigerated Liquid USP

PACKAGE LABEL

Bulk Carbon Dioxide USP Certificate of Analysis
This is to certify that the carbon dioxide tested at MESSER PLANT on 10/27/2025, meets the United States Pharmacopoeia (USP) specifications, the requirements of Federal Specifications BB-C-101 Grade A and QVL E of CGA G6.2. This product was manufactured at a facility registered with the Federal Food and Drug Administration and is approved for prescription drug use. This product is not guaranteed to meet any other specification or intended for pesticide use. NDA 205815 NADA 141371
Furthermore, batch number 5784-A-102725-01, and lot number TCO2002-102725-13, which was loaded on 10/27/2025 and produced at MESSER PLANT comprises this shipment and was analyzed as shown below.
Analytical results are generated using USP monograph or validated equivalent methods.
FOR MEDICAL USE
Requirement Analytical Method Limit of Detection¹ Specification Limit Result
Carbon Dioxide Assay (CO₂) Speed of Sound 99.99% 99.0% 99.99%
Nitrogen Oxide (NO) IMR-MS 0.05 ppm 2.5 ppm ND
Nitrogen Dioxide (NO₂) IMR-MS 0.1 ppm 2.5 ppm ND
Ammonia (NH₃) IMR-MS 0.03 ppm 25 ppm ND
Sulfur Dioxide (SO₂) IMR-MS 0.03 ppm 5 ppm ND
Hydrogen Sulfide (H₂S) IMR-MS 0.03 ppm 1 ppm ND
Carbon Monoxide (CO) FTIR 0.05 ppm 10 ppm ND
Moisture (H₂O) Quartz Crystal 0.5 ppm 200 ppm 0.77 ppm
Notes:
1. Positive Carbon Dioxide Identification is achieved when the Assay results demonstrate meeting the specification.
2. The limit of detection (LOD) for each test method is the threshold value for results to be reported with certainty in the accuracy of results. A test result outside the detection limit for the test method will be reported as ND.
3. ND = None Detected
4. ppm = parts per million by volume, ppb = parts per billion by volume, 1 ppm = 1,000 ppb
Product analyzed using Messer Ultra Guard Suite
Certified By:
On:
(Signature) (Date)
John Doe
(Print Name & Title)
On behalf of Messer